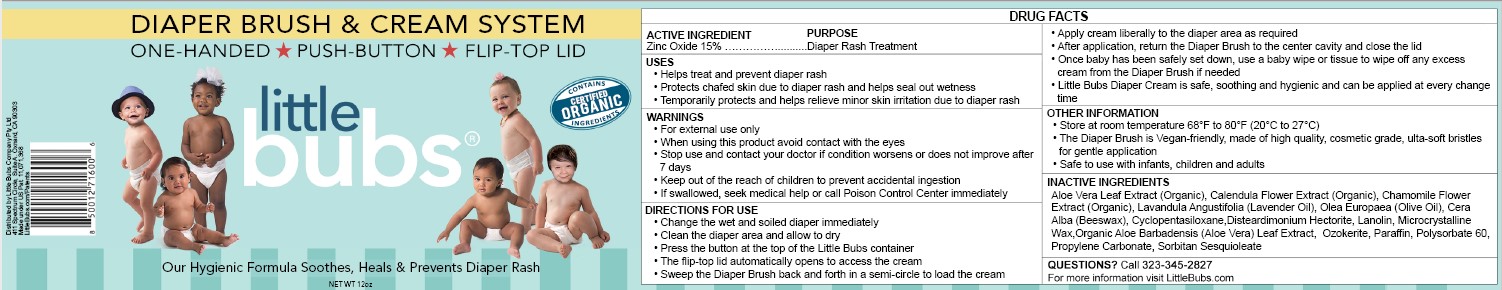 DRUG LABEL: LITTLE BUBS DIAPER
NDC: 72849-101 | Form: CREAM
Manufacturer: LITTLE BUBS COMPANY PTY LTD
Category: otc | Type: HUMAN OTC DRUG LABEL
Date: 20240109

ACTIVE INGREDIENTS: ZINC OXIDE 15.25 g/100 g
INACTIVE INGREDIENTS: YELLOW WAX; CYCLOMETHICONE 5; DISTEARDIMONIUM HECTORITE; LANOLIN; LAVENDER OIL; MICROCRYSTALLINE WAX; OLIVE OIL; ALOE VERA LEAF; CALENDULA OFFICINALIS FLOWER; CHAMOMILE; CERESIN; PARAFFIN; POLYSORBATE 60; PROPYLENE CARBONATE; SORBITAN SESQUIOLEATE

LITTLE BUBS - DIAPER BRUSH AND CREAM (72849-101)

ACTIVE INGREDIENT

ZINC OXIDE 15.25%

PURPOSE

SKIN PROTECTANT

USES

- HELPS TREAT AND PREVENT DIAPER RASH
- PROTECTS CHAFED SKIN DUE TO DIAPER RASH AND HELPS SEAL OUT WETNESS

WARNINGS

- FOR EXTERNAL USE ONLY
- WHEN USING THIS PRODUCT AVOID CONTACT WITH THE EYES
- STOP USE AND ASK A DOCTOR IF CONDITION WORSENS OR DOES NOT IMPROVE AFTER 7 DAYS
- KEEP OUT OF REACH OF CHILDREN TO PREVENT ACCIDENTAL INGESTION
- IF SWALLOWED, SEEK MEDICAL HELP OR CALL PIOSON CONTROL CENTER IMMEDIATELY

- KEEP OUT OF REACH OF CHILDREN TO PREVENT ACCIDENTAL INGESTION
- IF SWALLOWED, SEEK MEDICAL HELP OR CALL PIOSON CONTROL CENTER IMMEDIATELY

DIRECTIONS

- REMOVE SEAL FROM CONTAINER PRIOR TO USE
- CHANGE WET AND SOILED DIAPER IMMEDIATELY
- CLEANSE THE DIAPER AREA AND ALLOW TO DRY
- PUSH BUTTON TO ACCESS CREAM. SWEEP THE APPLICATOR BRUSH MOVING THE BRISTLES BACK AND FORTH IN A SEMI-CIRCLE LOADING CREAM ONTO YOUR DIAPER BRUSH AS REQUIRED
- APPLY CREAM LIBERALLY AND AS OFTEN AS NECESSARY WITH EACH DIAPER CHANGE AND ESPECIALLY WHEN EXPOSED TO WET DIAPERS FOR A PROLONGED PERIOD OF TIME, SUCH AS BEDTIME
- RETURN YOUR DIAPER BRUSH TO ITS CENTER CAVITY AND CLOSE THE LID. ONCE BABY HAS BEEN SAFELY SET DOWN, USE A BABY WIPE OR TISSUE TO SPOT CLEAN YOUR DIAPER BRUSH IF REQUIRED.

OTHER INFORMATION

- STORE AT ROOM TEMPERATURE 20C TO 27C (68F TO 80F)
- USE WITH INFANTS, CHILDREN AND ADULTS

INACTIVE INGREDIENTS

CERA ALBA (BEESWAX), CYCLOPENTASILOXANE, DISTEARDIMONIUM HECTORITE, LANOLIN, LAVANDULA ANGUSTIFOLIA (LAVENDER) OIL, MICROCRYSTALLINE WAX, OLEA EUROPAEA (OLIVE) OIL, ORGANIC ALOE BARBADENSIS (ALOE VERA) LEAF EXTRACT, ORGANIC CALENDULA OFFICINALIS (CALENDULA) FLOWER EXTRACT, ORGANIC MATRICARIA RECUTITA (CHAMOMILE) FLOWER EXTRACT, OZOKERITE, PARAFFIN WAX, POLYSORBATE 60, PROPYLENE CARBONATE, SORBITAN SESQUIOLEATE